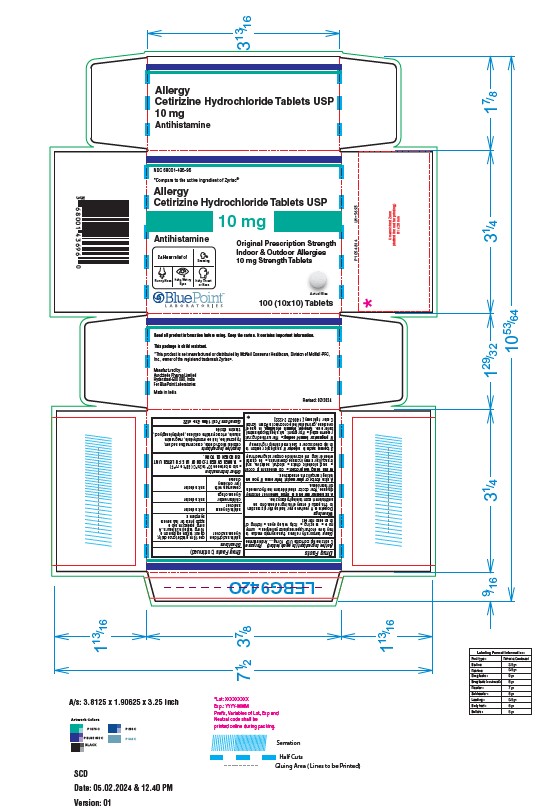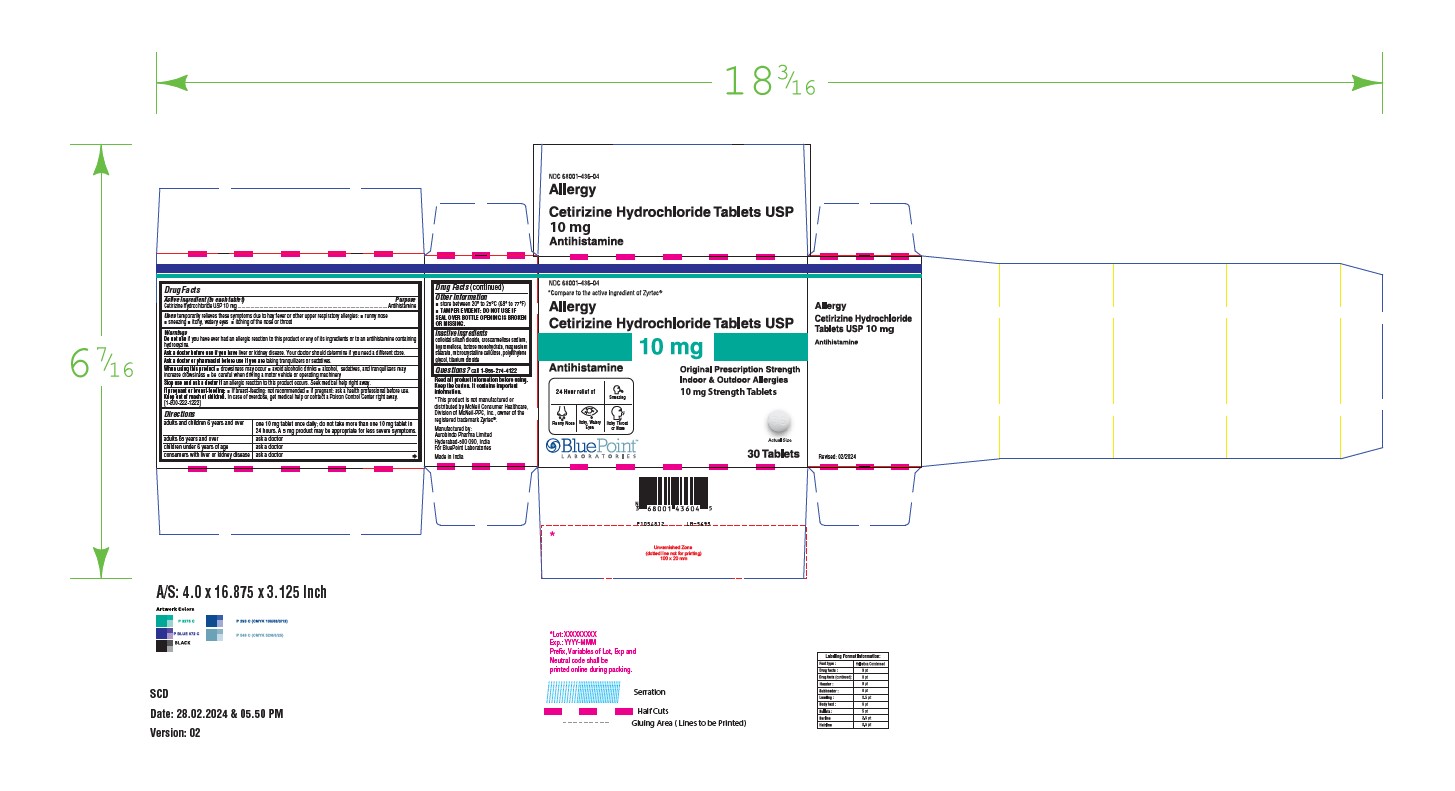 DRUG LABEL: Cetirizine Hydrochloride (Allergy)
NDC: 68001-436 | Form: TABLET
Manufacturer: BluePoint Laboratories
Category: otc | Type: HUMAN OTC DRUG LABEL
Date: 20251030

ACTIVE INGREDIENTS: CETIRIZINE HYDROCHLORIDE 10 mg/1 1
INACTIVE INGREDIENTS: SILICON DIOXIDE; CROSCARMELLOSE SODIUM; HYPROMELLOSE 2910 (5 MPA.S); LACTOSE MONOHYDRATE; MAGNESIUM STEARATE; MICROCRYSTALLINE CELLULOSE; POLYETHYLENE GLYCOL 400; TITANIUM DIOXIDE

CETIRIZINE HCL Tablets USP

Drug Facts

Active ingredient (in each tablet)

For 10 mg:
Cetirizine hydrochloride USP 10 mg

Purpose

Antihistamine

Uses

temporarily relieves these symptoms due to hay fever or other upper respiratory allergies:

- runny nose
- sneezing
- itchy, watery eyes
- itching of the nose or throat

Warnings

Do not use if you have ever had an allergic reaction to this product or any of its ingredients or to an antihistamine containing hydroxyzine.

Ask a doctor before use if you have

liver or kidney disease. Your doctor should determine if you need a different dose.

Ask a doctor or pharmacist before use if you are

taking tranquilizers or sedatives.

When using this product

- drowsiness may occur
- avoid alcoholic drinks
- alcohol, sedatives, and tranquilizers may increase drowsiness
- be careful when driving a motor vehicle or operating machinery

Stop use and ask a doctor if

an allergic reaction to this product occurs. Seek medical help right away.

If pregnant or breast-feeding:

- If breast-feeding: not recommended
- if pregnant: ask a health professional before use.

Keep out of reach of children.

In case of overdose, get medical help or contact a Poison Control Center right away. [1-800-222-1222]

Directions

For 10 mg:

adults and children 6 years and over | one 10 mg tablet once daily; do not take more than one 10 mg tablet in 24 hours. A 5 mg product may be appropriate for less severe symptoms.
adults 65 years and over | ask a doctor
children under 6 years of age | ask a doctor
consumers with liver or kidney disease | ask a doctor

Other information

- store between 20° to 25°C (68° to 77°F)
- TAMPER EVIDENT: DO NOT USE IF SEAL OVER BOTTLE OPENING IS BROKEN OR MISSING.

Inactive ingredients

colloidal silicon dioxide, croscarmellose sodium, hypromellose, lactose monohydrate, magnesium stearate, microcrystalline cellulose, polyethylene glycol, titanium dioxide.

Questions?

call 1-855-274-4122
Manufactured by:
Aurobindo Pharma Limited
Hyderabad-500 090, India
For BluePoint Laboratories
Made in India
Code: TS/DRUGS/19/1993

Issued 05/2020

PACKAGE LABEL-PRINCIPAL DISPLAY PANEL - 10 mg (30's Tablet Container Carton Label)

NDC 68001-436-04
*Compare to the active
ingredient of Zyrtec®
Allergy Relief
Cetirizine Hydrochloride Tablets USP 10 mg
Antihistamine
Original Prescription Strength
Indoor & Outdoor Allergies
24 Hour Relief of :

- Sneezing
- Runny Nose
- Itchy, Watery Eyes
- Itchy Throat or Nose

30 Tablets
10 mg each

PACKAGE LABEL-PRINCIPAL DISPLAY PANEL - 10 mg (10 x 10 Blister Carton Label)

NDC68001-436-96
*Compare to the active
ingredient of Zyrtec®
Allergy Relief
Cetirizine Hydrochloride Tablets USP 10 mg
Antihistamine
Original Prescription Strength
Indoor & Outdoor Allergies
24 Hour Relief of :

- Sneezing
- Runny Nose
- Itchy, Watery Eyes
- Itchy Throat or Nose

100 (10x10) Tablets
10 mg each